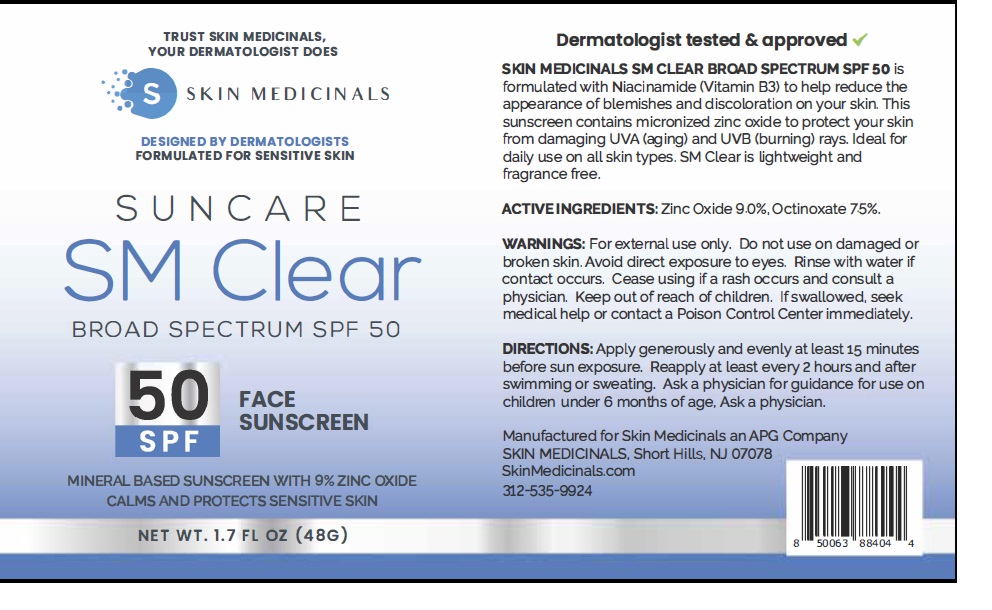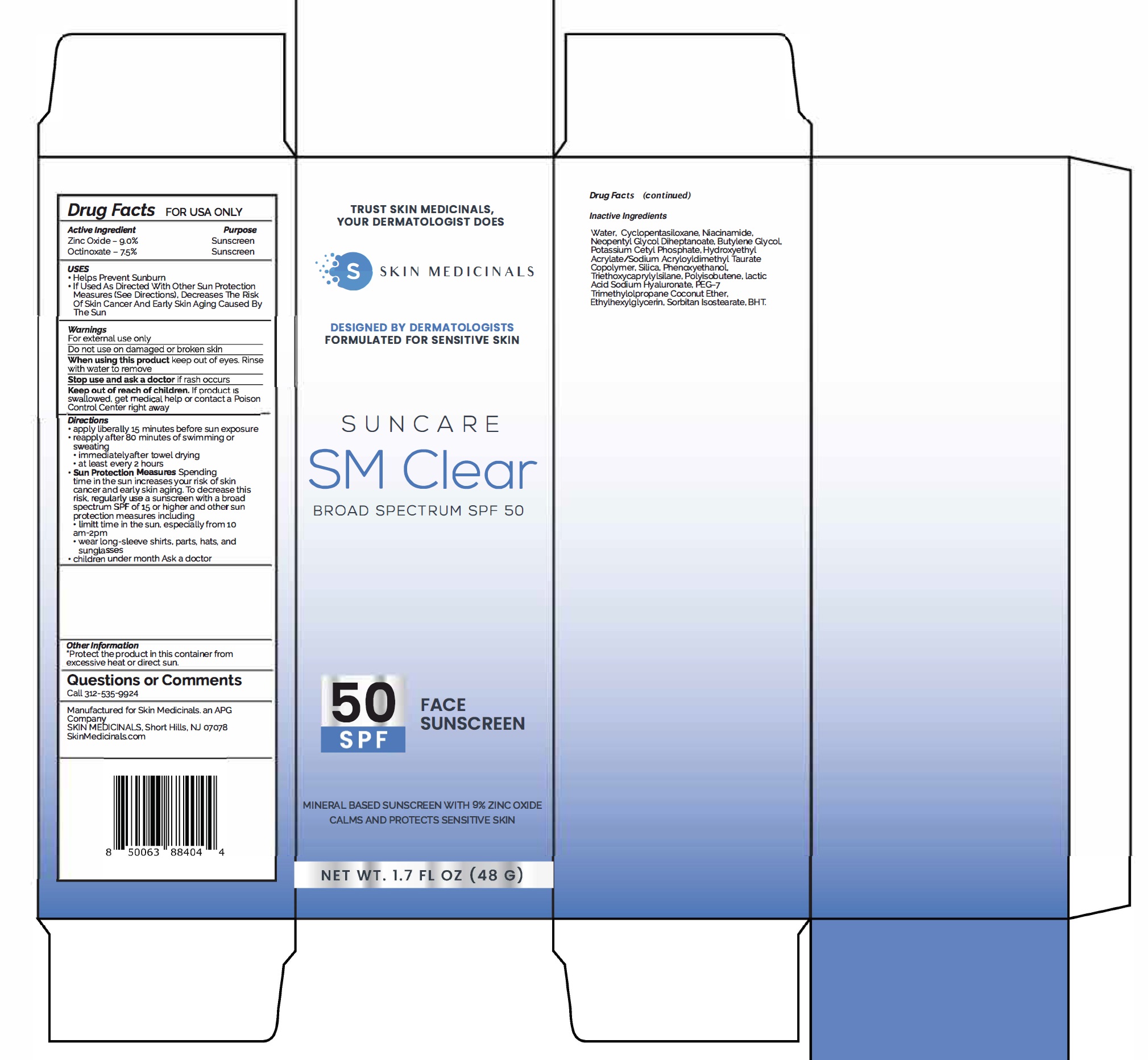 DRUG LABEL: Skin Medicinals SM Clear Broad Spectrum SPF 50
NDC: 85748-001 | Form: CREAM
Manufacturer: SKIN MEDICINALS LLC
Category: otc | Type: HUMAN OTC DRUG LABEL
Date: 20250501

ACTIVE INGREDIENTS: ZINC OXIDE 90 mg/1 mL; OCTINOXATE 75 mg/1 mL
INACTIVE INGREDIENTS: WATER; CYCLOMETHICONE 5; NIACINAMIDE; NEOPENTYL GLYCOL DIHEPTANOATE; BUTYLENE GLYCOL; POTASSIUM CETYL PHOSPHATE; SILICON DIOXIDE; PHENOXYETHANOL; TRIETHOXYCAPRYLYLSILANE; LACTIC ACID, UNSPECIFIED FORM; HYALURONATE SODIUM; PEG-7 TRIMETHYLOLPROPANE COCONUT ETHER; ETHYLHEXYLGLYCERIN; SORBITAN ISOSTEARATE; BUTYLATED HYDROXYTOLUENE

Skin Medicinals SM Clear Broad Spectrum SPF 50

Active Ingredient

Zinc Oxide - 9.0%

Octinoxate - 7.5%

Purpose

Sunscreen

USES

- Helps Prevent Sunburn
- If Used As Directed With Other Sun Protection Measures (See Directions), Decreases The Risk Of Skin cancer And Early Skin Aging Caused By The Sun

Warnings

For external use only

Do not use

on damaged or broken skin

When using this product

keep out of eyes. Rinse with water to remove

Stop use and ask a doctor

if rash occurs

Keep out of reach of children.

If product is swallowed, get medical help or contact a Poison Control Center right away

Directions

- apply liberally 15 minutes before sun exposure
- reapply after 80 minutes of swimming or sweating
- immediatelyafter towel drying
- at least every 2 hours
- Sun protectlon MeasuresSpending time In the sun increases your risk of skin cancer and early skin aging. To decrease this risk, regularly use a sunscreen with broad spectrum SPF of 15 or higher and other sun protection measures including
- limit time in the sun, especially from 10 am-2pm
- wear Long-sleeve shirts, parts, hats, and sunglasses
- children under month Ask a doctor

Other Information

"Protect the product In this container from excessive heat or direct sun.

Questions or Comments

call 312-535-9924

Inactive Ingredients

Water, Cyclopentasiloxane, Niacinamide, Neopentyl Glycol Diheptanoate, Butylene Glycol, Potassium Cetyl Phosphate, Hydroxyethyl Acrylate/Sodium Acryloyldimethyl Taurate Copolymer, Silica, Phenoxyethanol, Triethoxycaprylylsilane, Polyisobutene, Lactic Acid Sodium Hyaluronate, PEG-7 Trimethylolpropane Coconut Ether, Ethylhexylglycerin, Sorbitan Isostearate, BHT.